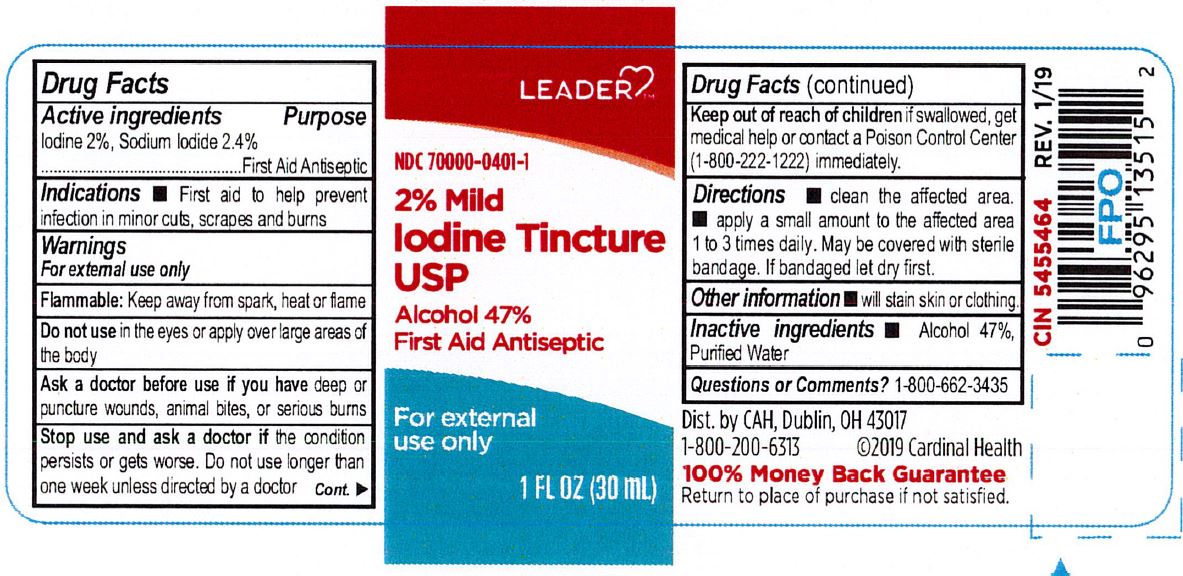 DRUG LABEL: LEADER 2% Mild Iodine Tincture
NDC: 70000-0401 | Form: LIQUID
Manufacturer: Cardinal Health, 110 dba Leader
Category: otc | Type: HUMAN OTC DRUG LABEL
Date: 20240513

ACTIVE INGREDIENTS: SODIUM IODIDE 24 mg/1 mL; IODINE 20 mg/1 mL
INACTIVE INGREDIENTS: WATER; ALCOHOL

LEADER 2% Mild Iodine Tincture

ACTIVE INGREDIENT

Iodine 2%

Sodium Iodide 2.4%

INDICATIONS AND USAGE

First aid to help prevent infection in minor cuts, scrapes, and burns.

WARNINGS

For external use only

Keep out of reach of children.If swallowed, get medical help or contact a Poison Control Center (1-800-222-1222) immediately.

DOSAGE AND ADMINISTRATION

Clearn the affected area

apply a small amount to the affected area 1 to 3 times daily. May be covered with sterile bandage. If bandaged let dry first.

PURPOSE

First Aid Antiseptic

INACTIVE INGREDIENT

Alcohol 47%

Purified Water